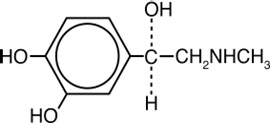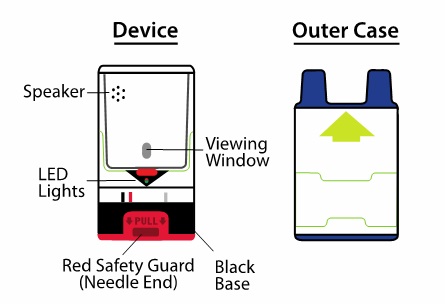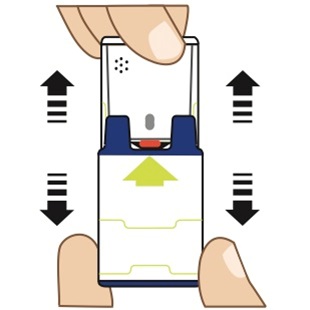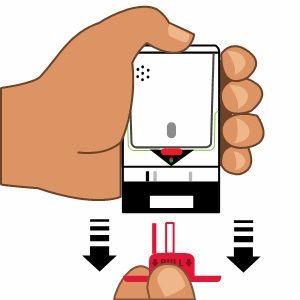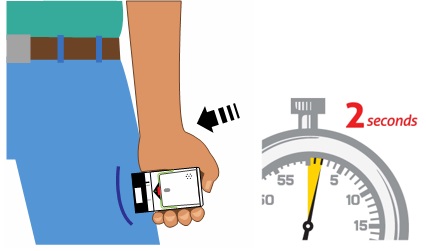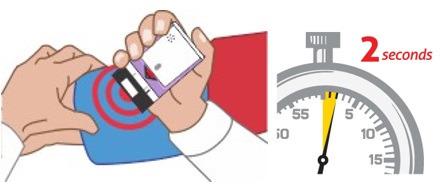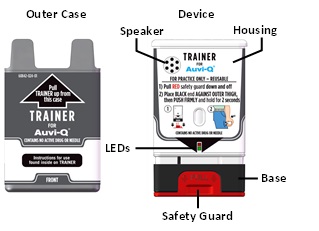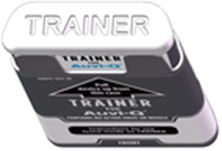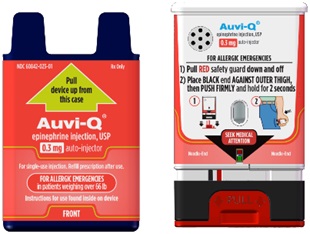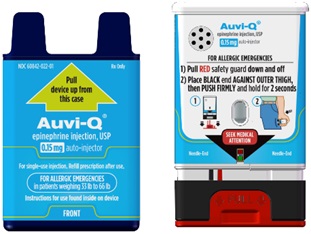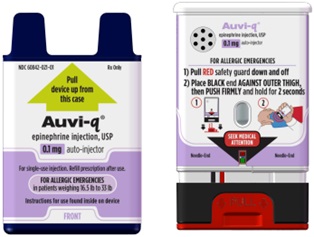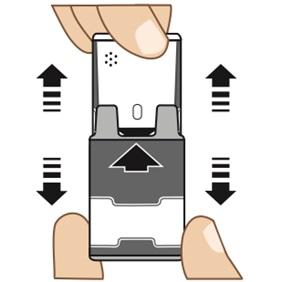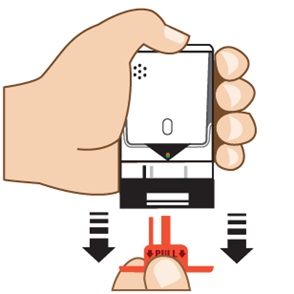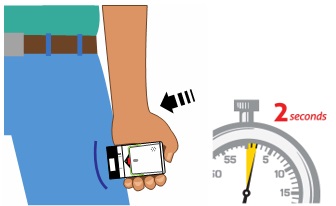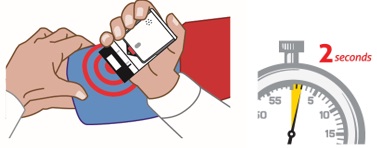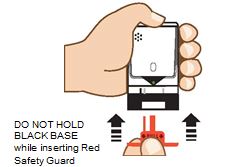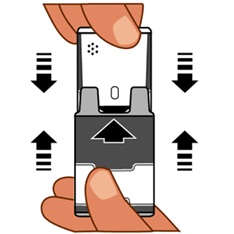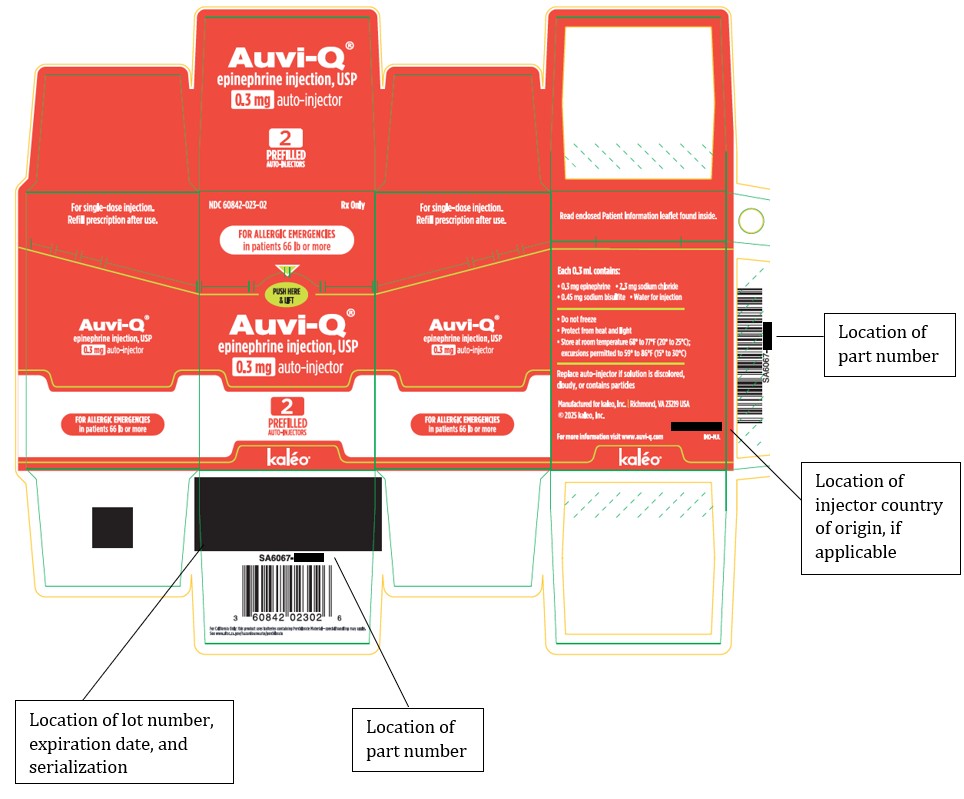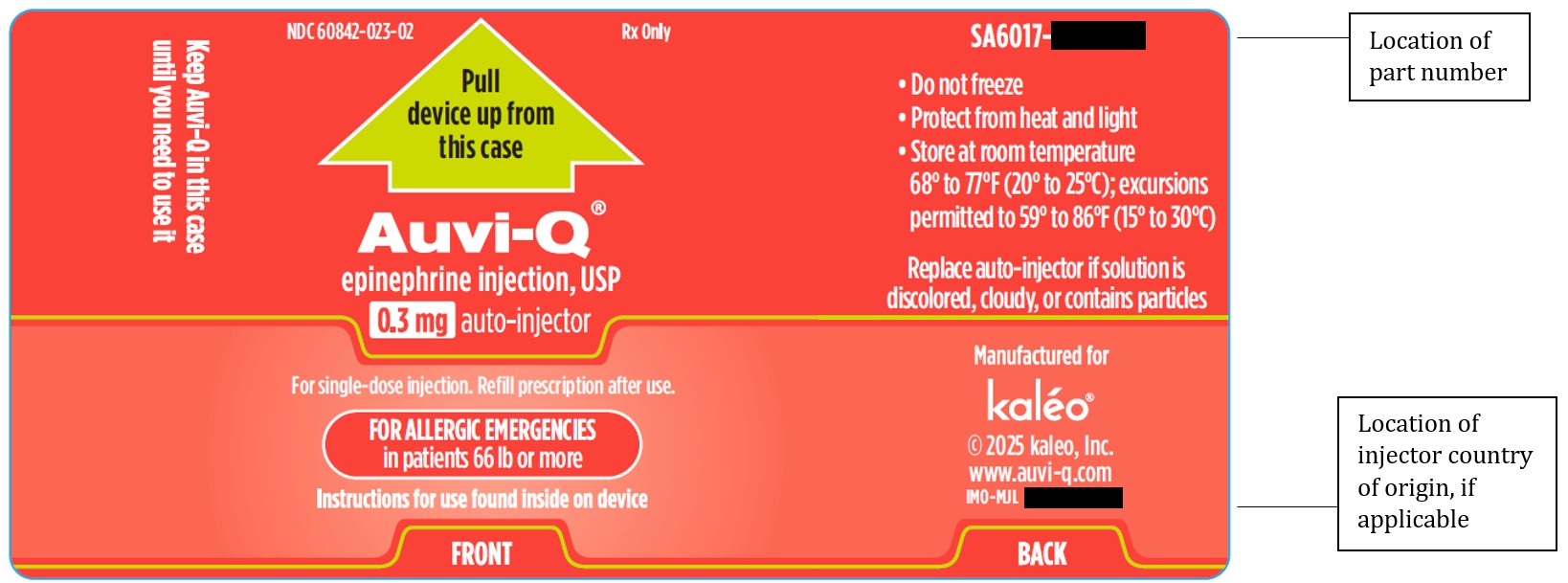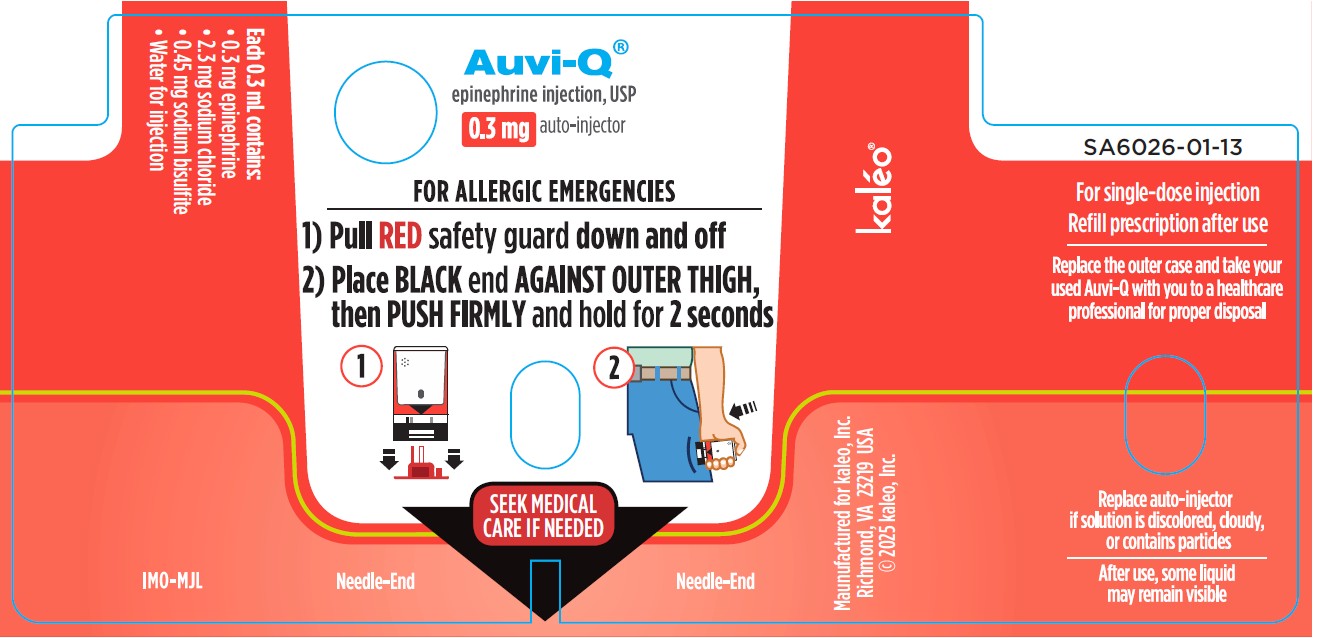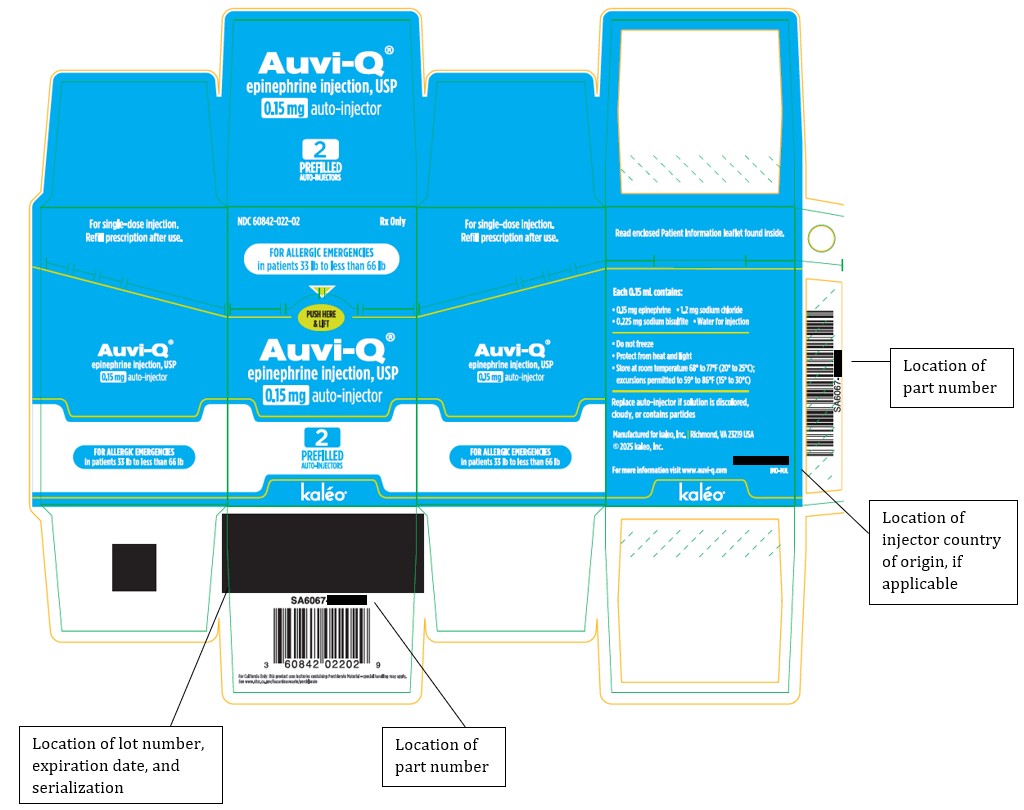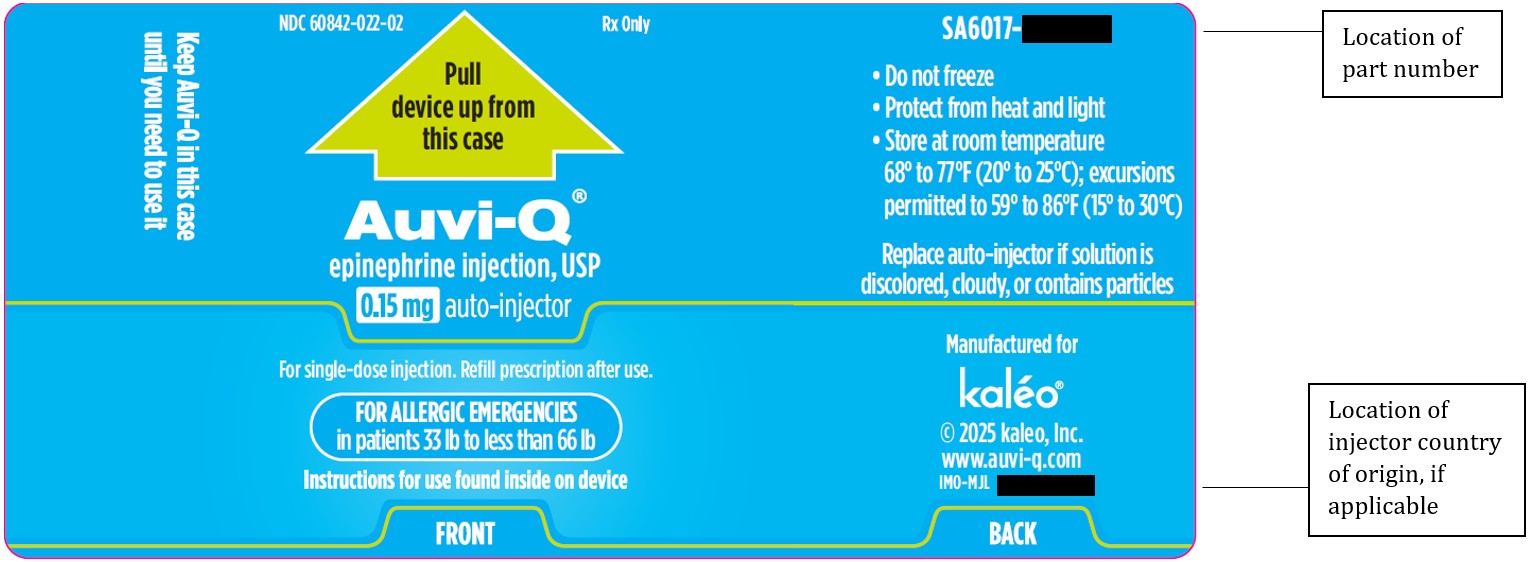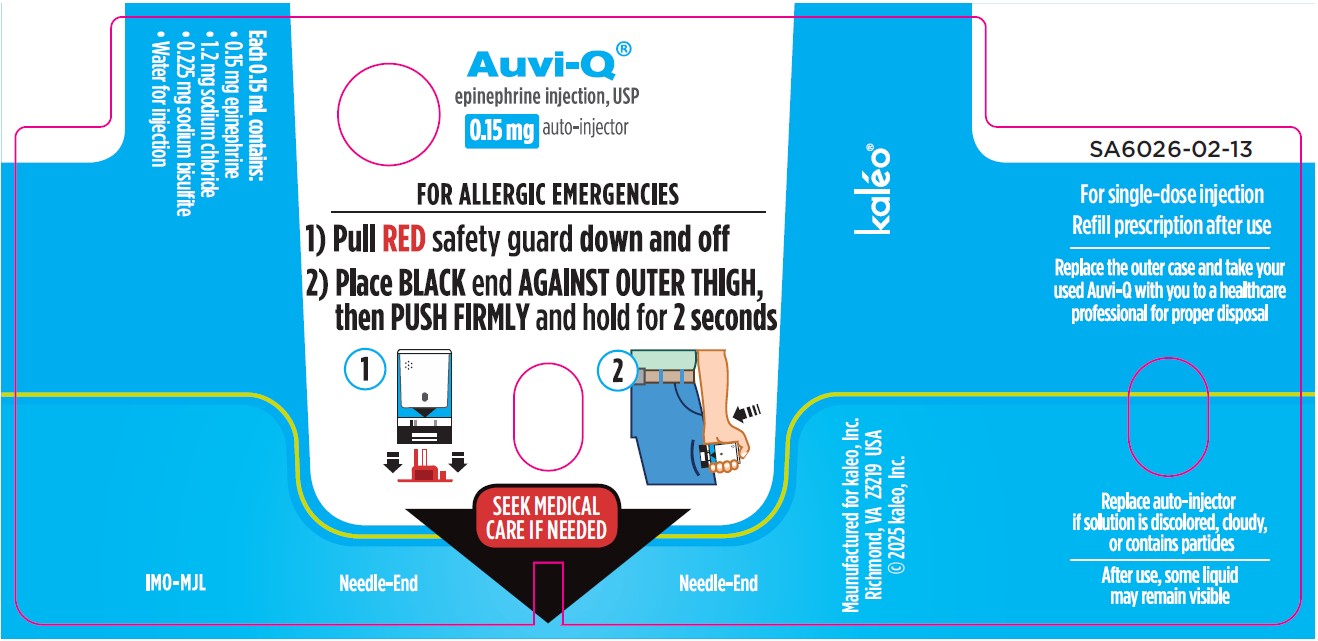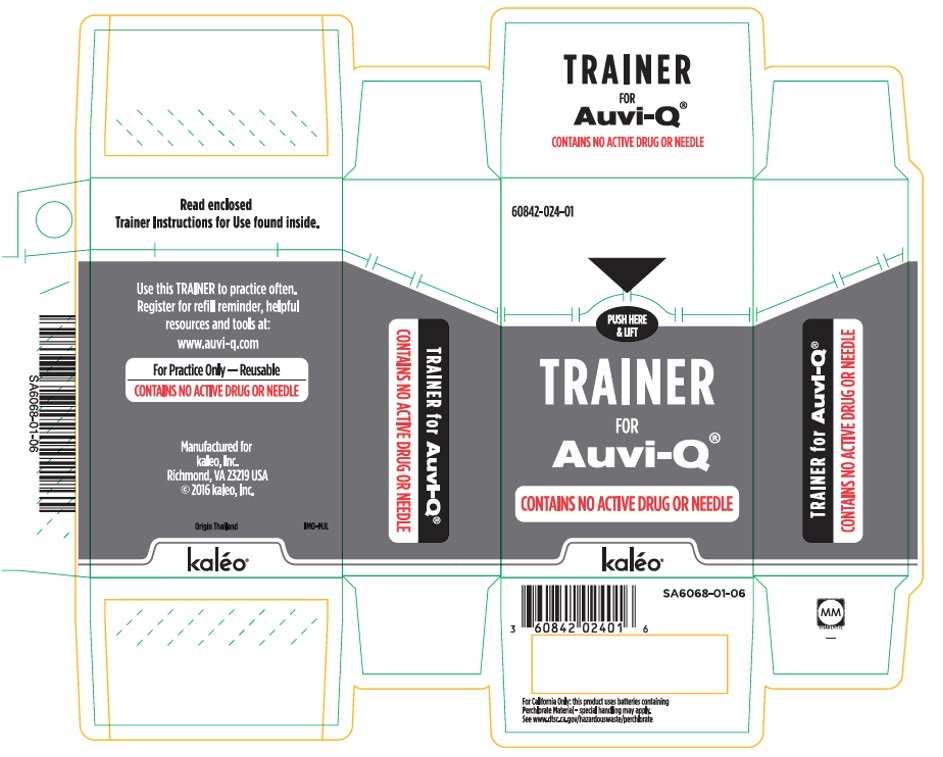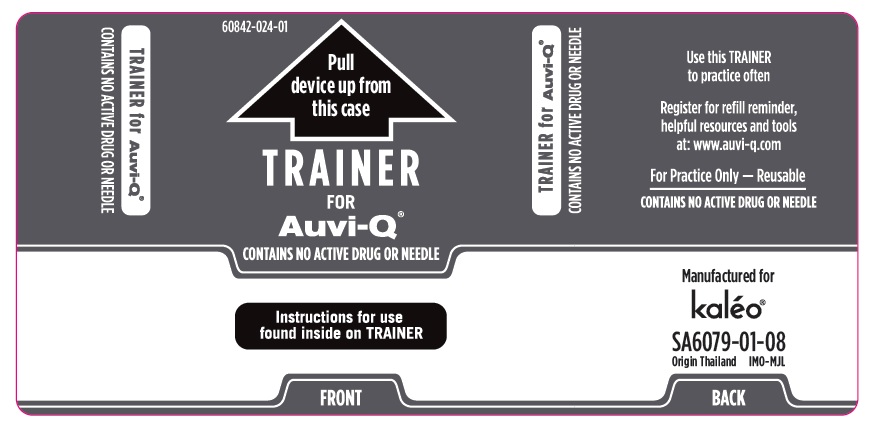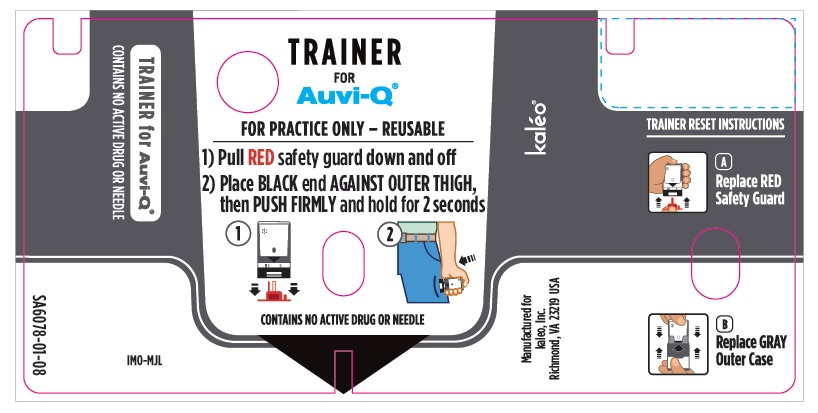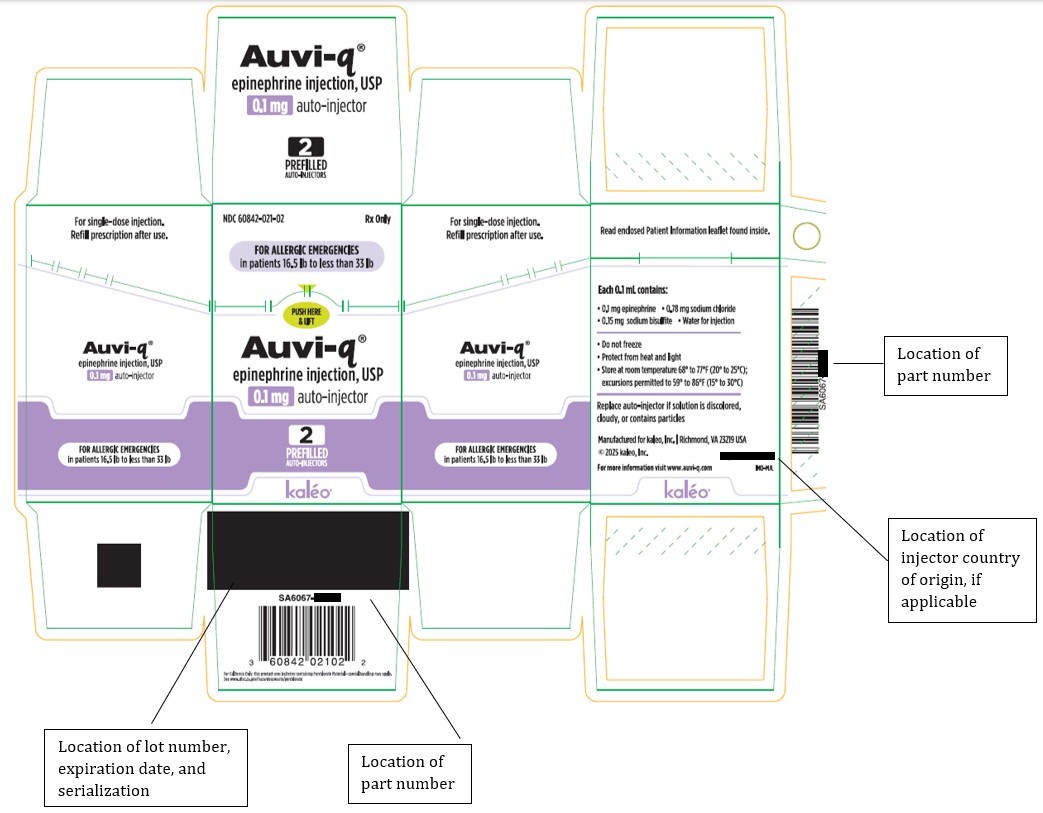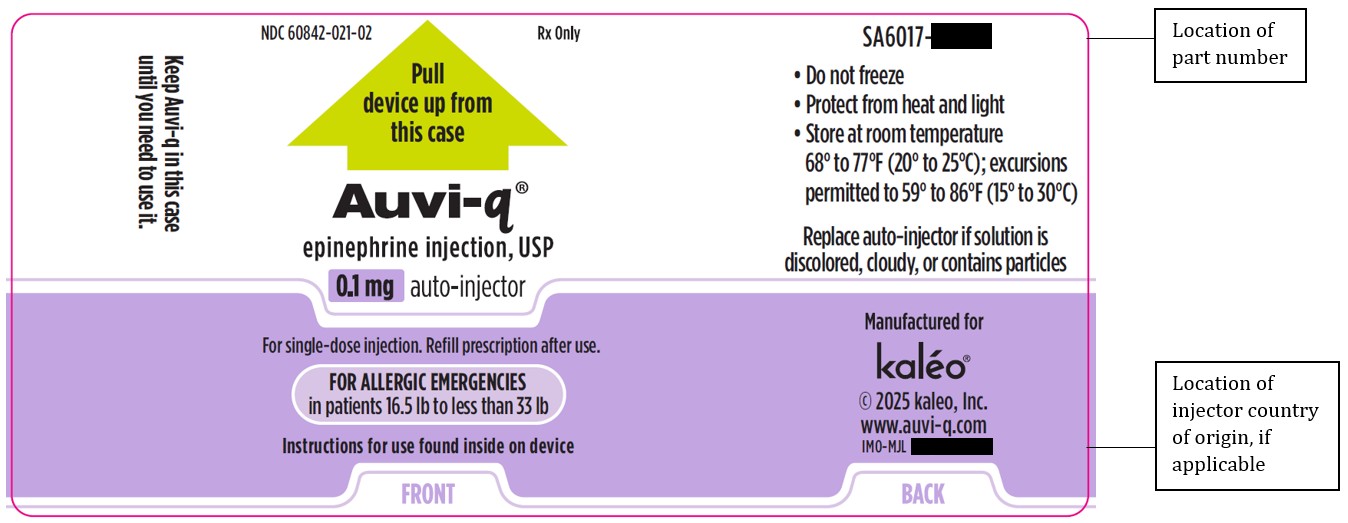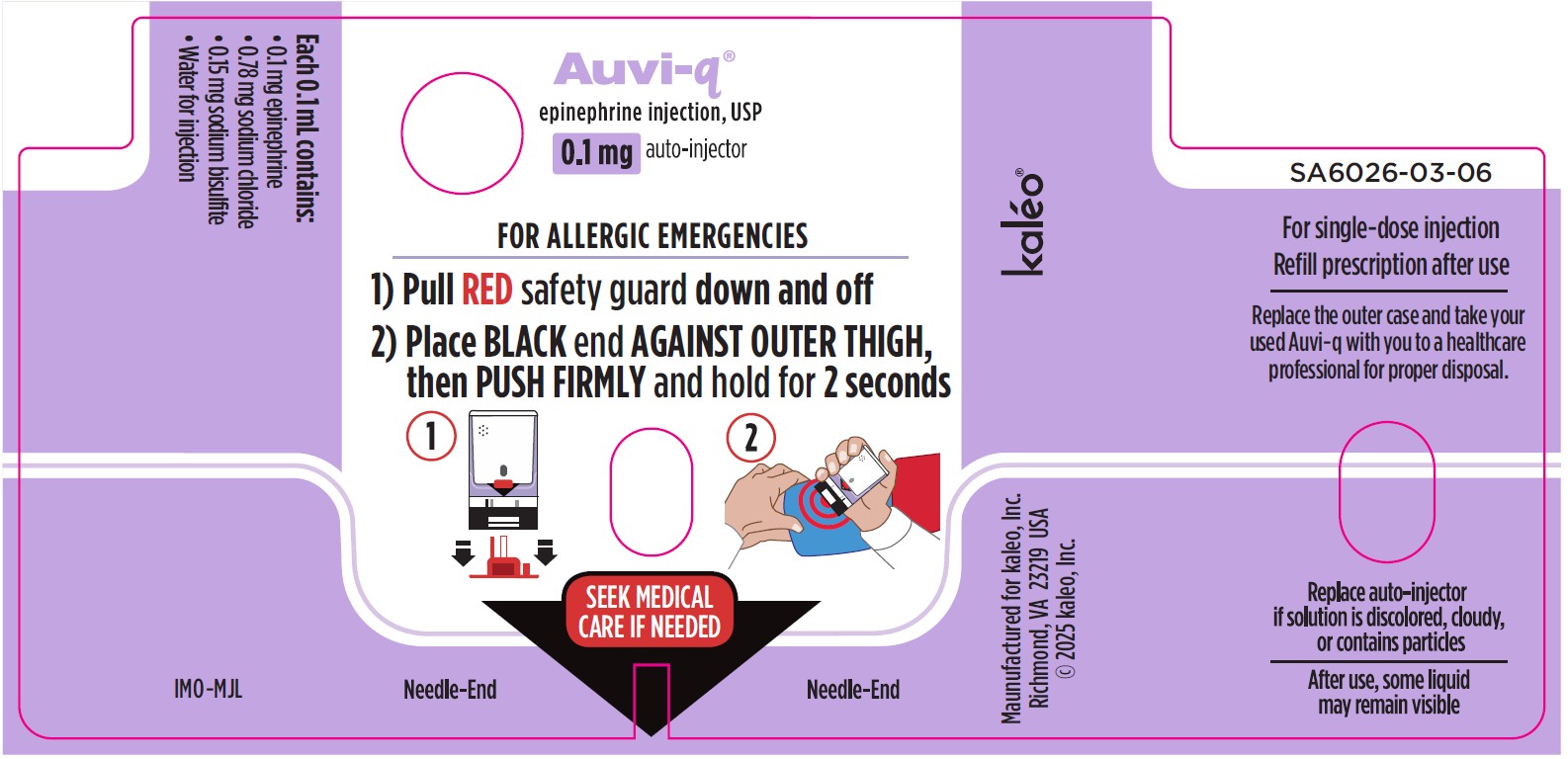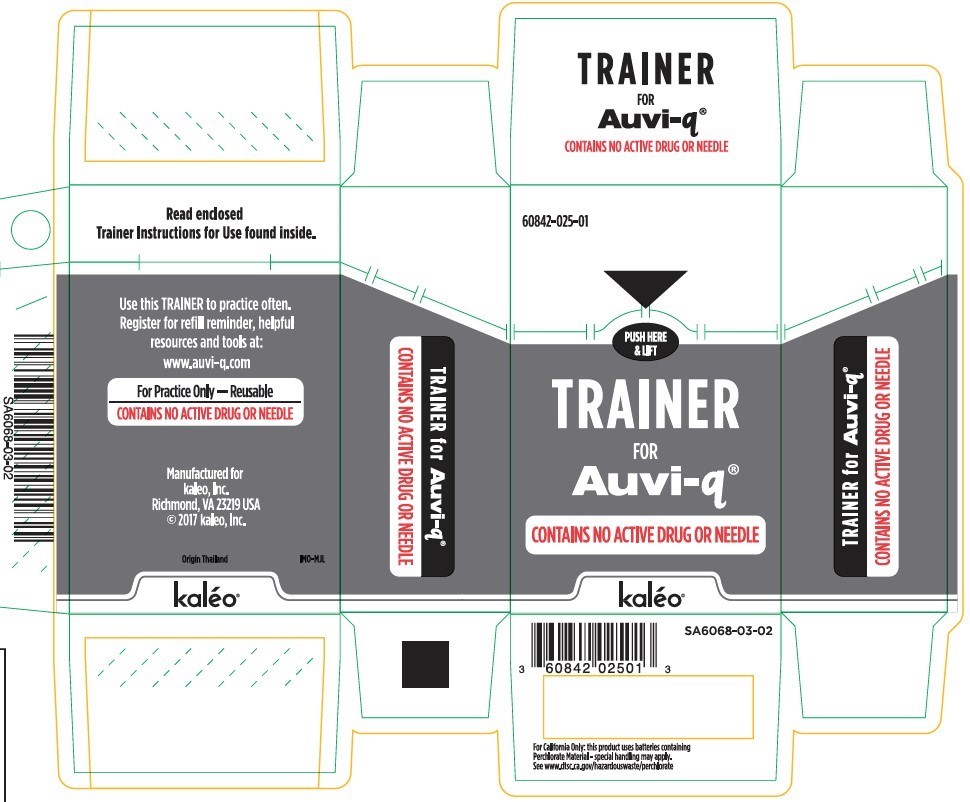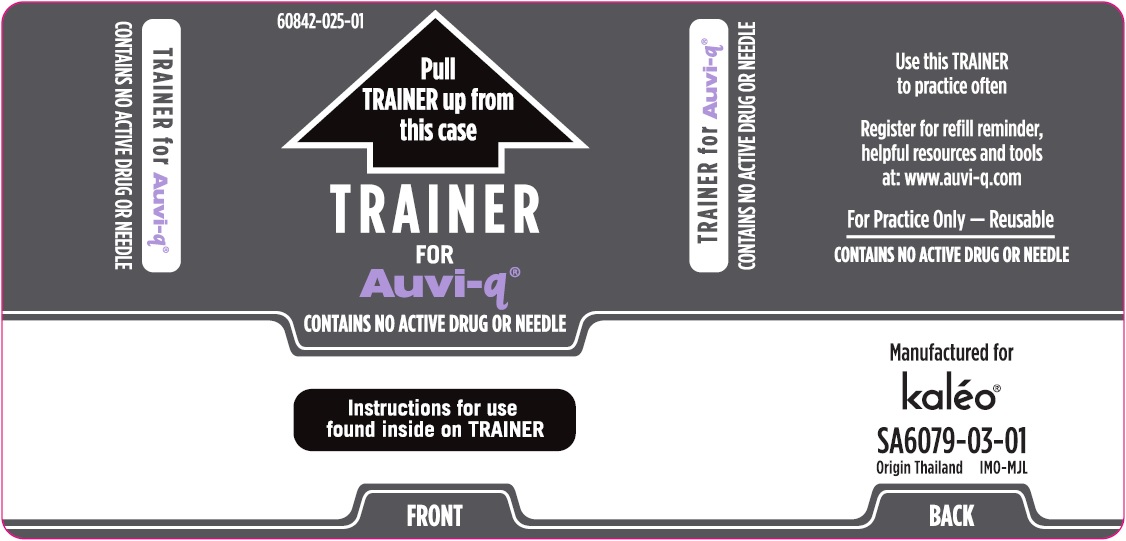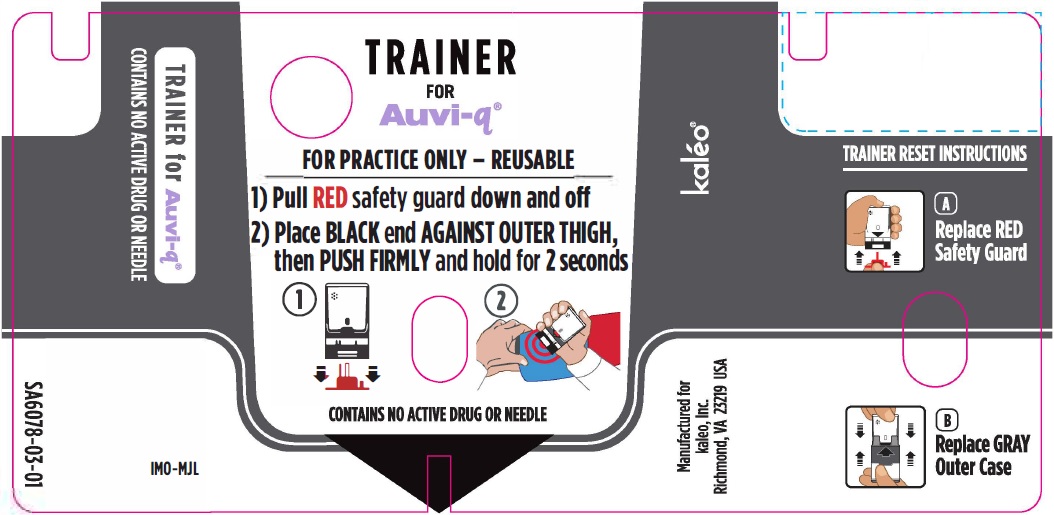 DRUG LABEL: Auvi-Q
NDC: 60842-023 | Form: INJECTION, SOLUTION
Manufacturer: kaleo, Inc
Category: prescription | Type: HUMAN PRESCRIPTION DRUG LABEL
Date: 20251002

ACTIVE INGREDIENTS: EPINEPHRINE 0.3 mg/0.3 mL
INACTIVE INGREDIENTS: SODIUM CHLORIDE  2.3 mg/0.3 mL; SODIUM BISULFITE 0.45 mg/0.3 mL; WATER; HYDROCHLORIC ACID 

HIGHLIGHTS OF PRESCRIBING INFORMATION

These highlights do not include all the information needed to use AUVI-Q® safely and effectively. See full prescribing information for AUVI-Q.
AUVI-Q® (epinephrine injection), for intramuscular or
subcutaneous use
Initial U.S. Approval: 1939

1 INDICATIONS AND USAGE

AUVI-Q is a non-selective alpha and beta-adrenergic receptor agonist indicated for the emergency treatment of type I allergic reactions, including anaphylaxis, in adult and pediatric patients who weigh 7.5 kg or greater. (1)

2 DOSAGE AND ADMINISTRATION

The recommended dosage of AUVI-Q is based on weight. (2.1) Administer AUVI-Q intramuscularly or subcutaneously into the anterolateral aspect of the thigh, through clothing if necessary. (2.2)

Recommended Dosage

Patient’s Weight | Dosage
30 kg or greater | AUVI-Q 0.3 mg
15 kg to less than 30 kg | AUVI-Q 0.15 mg
7.5 kg to less than 15 kg | AUVI-Q 0.1 mg

In the absence of clinical improvement or if symptoms worsen after the initial treatment, a second dose of AUVI-Q may be administered with a second autoinjector starting 5 minutes after the first dose. (2.1)

- Advise patients when to seek emergency medical assistance for close monitoring of the anaphylactic episode and in the event further treatment is required. (2.1)
- It is recommended that patients are prescribed and have immediate access to two AUVI-Q devices at all times. (2.1)
- See full prescribing information for administration instructions. (2.2)

3 DOSAGE FORMS AND STRENGTHS

Injection:

- 0.3 mg (0.3 mg/0.3 mL) epinephrine in a single-dose prefilled autoinjector (3)
- 0.15mg (0.15 mg/0.15 mL) epinephrine in a single-dose prefilled autoinjector (3)
- 0.1 mg (0.1 mg/0.1 mL) epinephrine in a single-dose prefilled autoinjector (3)

4 CONTRAINDICATIONS

None. (4)

5 WARNINGS AND PRECAUTIONS

- Do not inject intravenously, into buttock, digits, hands, or feet. (5.1)
- Hold the child’s leg firmly in place and limit movement prior to and during injection when administering to young children or infants to minimize the risk of injection-related injury. (5.1)
- Rare cases of serious skin and soft tissue infections have been reported following epinephrine injection. Advise patients to seek medical care if they develop signs or symptoms of infection. (5.2)
- Administer with caution in patients with heart disease; may aggravate angina pectoris or produce ventricular arrhythmias. (5.3)
- May aggravate certain coexisting conditions. (5.3)
- The presence of a sulfite in this product should not deter use. (5.4)

6 ADVERSE REACTIONS

Adverse reactions to epinephrine include anxiety, apprehensiveness, restlessness, tremor, weakness, dizziness, sweating, palpitations, pallor, nausea and vomiting, headache, and/or respiratory difficulties. (6)

To report SUSPECTED ADVERSE REACTIONS, contact kaleo, Inc. at 1-877-302-8847 or FDA at 1-800-FDA-1088 or www.fda.gov/medwatch.

7 DRUG INTERACTIONS

- Cardiac glycosides, diuretics, or anti-arrhythmics: observe for development of cardiac arrhythmias. (7.1)
- Tricyclic antidepressants, monoamine oxidase inhibitors, levothyroxine sodium, certain antihistamines, and catechol-O-methyl transferase inhibitors may potentiate effects of epinephrine. (7.2)
- Beta-adrenergic blocking drugs antagonize cardiostimulating and bronchodilating effects of epinephrine. (7.3)
- Alpha-adrenergic blocking drugs antagonize vasoconstricting and hypertensive effects of epinephrine. (7.3)
- Ergot alkaloids may reverse the pressor effects of epinephrine. (7.3)

8 USE IN SPECIFIC POPULATIONS

Elderly patients may be at greater risk of developing adverse reactions. (8.5)

FULL PRESCRIBING INFORMATION

1 INDICATIONS AND USAGE

AUVI-Q is indicated for the emergency treatment of type I allergic reactions, including anaphylaxis, in adult and pediatric patients who weigh 7.5 kg or greater.

2 DOSAGE AND ADMINISTRATION

2.1 Recommended Dosage

The recommended dosage for patients who weigh 7.5 kg or greater is based on weight and the dosage is provided in Table 1. Administer AUVI-Q intramuscularly or subcutaneously into the anterolateral aspect of the thigh.

Table 1. Recommended Dosage of AUVI-Q Based on Patient’s Weight

Patient’s Weight | Dosage
30 kg or greater | AUVI-Q 0.3 mg
15 kg to less than 30 kg | AUVI-Q 0.15 mg
7.5 kg to less than 15 kg | AUVI-Q 0.1 mg

- Since the doses of epinephrine delivered from AUVI-Q are fixed, use other forms of injectable epinephrine if doses lower than 0.1 mg are deemed necessary.
- In the absence of clinical improvement or if symptoms worsen after the initial treatment, a second dose of AUVI-Q may be administered with a second autoinjector starting 5 minutes after the first dose.
- Advise patients when to seek emergency medical assistance for close monitoring of the anaphylactic episode and in the event further treatment is required.
- It is recommended that patients are prescribed and have immediate access to two AUVI-Q devices at all times.

2.2 Administration Instructions

- Each AUVI-Q contains a single dose of epinephrine for single use.
- Visually inspect the epinephrine solution in the viewing window of AUVI-Q for particulate matter, cloudiness, and discoloration prior to administration.
- Instruct caregivers of young children and infants who are prescribed AUVI-Q and who may be uncooperative and kick or move during an injection to hold the child’s leg firmly in place and limit movement prior to and during an injection [see Warnings and Precautions (5.1)].
- Inject AUVI-Q intramuscularly or subcutaneously into the anterolateral aspect of the thigh, through clothing if necessary. Do not inject intravenously, and do not inject into buttocks, digits, hands or feet [see Warnings and Precautions (5.1)].
- If a second dose is needed, administer a new AUVI-Q starting 5 minutes after the first dose. More than two sequential doses of epinephrine should be administered under direct medical supervision. Refer patients and caregivers to the Instructions for Use for detailed administration instructions.

3 DOSAGE FORMS AND STRENGTHS

Injection:

- 0.3 mg (0.3 mg/0.3 mL) epinephrine injection, USP, clear and colorless solution, single-dose prefilled autoinjector
- 0.15 mg (0.15 mg/0.15 mL) epinephrine injection, USP, clear and colorless solution, single-dose prefilled autoinjector
- 0.1 mg (0.1 mg/0.1 mL) epinephrine injection, USP, clear and colorless solution, single-dose prefilled autoinjector

4 CONTRAINDICATIONS

None.

5 WARNINGS AND PRECAUTIONS

5.1 Injection-Related Complications

AUVI-Q should only be injected into the anterolateral aspect of the thigh [see Dosage and Administration (2.1, 2.2)].

- Do not inject intravenously. Large doses or accidental intravenous injection of epinephrine may result in cerebral hemorrhage due to sharp rise in blood pressure. Rapidly acting vasodilators can counteract the marked pressor effects of epinephrine for this inadvertent administration.
- Do not inject into buttock. Injection into the buttock may not provide effective treatment of anaphylaxis. If AUVI-Q is injected into the buttock, advise the patient to administer a second dose of AUVI-Q into the anterolateral aspect of the thigh and if symptoms worsen or persist, then go immediately to the nearest emergency room for further treatment of anaphylaxis. Additionally, injection into the buttock has been associated with Clostridial infections (gas gangrene). Cleansing with alcohol does not kill bacterial spores, and therefore, does not lower this risk.
- Do not inject into digits, hands or feet. Since epinephrine is a strong vasoconstrictor, accidental injection into the digits, hands or feet may result in loss of blood flow to the affected area and may not provide effective treatment of anaphylaxis. Advise the patient to administer a second dose of AUVI-Q into the anterolateral aspect of the thigh if experiencing anaphylaxis and then go immediately to the nearest emergency room and inform the healthcare provider in the emergency room of the location of the accidental injection. Treatment of such inadvertent administration should consist of vasodilation, in addition to further appropriate treatment of anaphylaxis [see Adverse Reactions (6)].
- Hold leg firmly during injection. To minimize the risk of injection-related injury when administering AUVI-Q to young children or infants, instruct caregivers to hold the child’s leg firmly in place and limit movement prior to and during injection.

5.2 Serious Infections at the Injection Site

Rare cases of serious skin and soft tissue infections, including necrotizing fasciitis and myonecrosis caused by Clostridia (gas gangrene), have been reported at the injection site following epinephrine injection for anaphylaxis. Clostridium spores can be present on the skin and introduced into the deep tissue with subcutaneous or intramuscular injection. While cleansing with alcohol may reduce the presence of bacteria on the skin, alcohol cleansing does not kill Clostridium spores. To decrease the risk of Clostridium infection, do not inject AUVI-Q into the buttock [see Warnings and Precautions (5.1)]. Advise patients to seek medical care if they develop signs or symptoms of infection, such as persistent redness, warmth, swelling, or tenderness, at the epinephrine injection site.

5.3 Risk Associated with Use of Epinephrine in Certain Coexisting Conditions

Some patients may be at greater risk for developing adverse reactions after epinephrine administration. Despite these concerns, the presence of these conditions is not a contraindication to epinephrine administration in an acute, life-threatening situation. Therefore, instruct patients with these conditions, and/or caregivers to the circumstances under which epinephrine should be used.

Administer epinephrine with caution to patients who have heart disease, including patients with cardiac arrhythmias, coronary artery disease, or hypertension. In such patients, or in patients who are on drugs that may sensitize the heart to arrhythmias, epinephrine may precipitate or aggravate angina pectoris as well as produce ventricular arrhythmias [see Drug Interactions (7) and Adverse Reactions (6)].

Epinephrine can temporarily exacerbate the underlying conditions or increase symptoms in patients with the following: hyperthyroidism, Parkinson’s disease, diabetes, renal impairment. Administer epinephrine with caution in patients with these conditions, including elderly patients and pregnant women.

5.4 Allergic Reactions Associated with Sulfite

Epinephrine is the preferred treatment for serious allergic reactions or other emergency situations even though AUVI-Q contains sodium bisulfite, a sulfite that may, in other products, cause allergic-type reactions including anaphylactic symptoms or life-threatening or less severe asthmatic episodes in certain susceptible persons. The alternatives to using epinephrine in a life-threatening situation may not be satisfactory. The presence of a sulfite in AUVI-Q should not deter administration of the drug for treatment of serious allergic or other emergency situations.

6 ADVERSE REACTIONS

The following clinically significant adverse reactions are described elsewhere in the labeling:

- Injection-Related Complications [see Warnings and Precautions (5.1)]
- Serious Infections at the Injection Site [see Warnings and Precautions (5.2)]
- Risks Associated with Use of Epinephrine in Certain Coexisting Conditions [see Warnings and Precautions (5.3)]
- Allergic Reactions Associated with Sulfite [see Warnings and Precautions (5.4)]

Adverse Reactions from Postapproval Use of Epinephrine Products

The following adverse reactions have been identified during postapproval use of epinephrine. Because these reactions are reported voluntarily from a population of uncertain size, it is not always possible to reliably estimate their frequency or establish a causal relationship to drug exposure.

Cardiovascular: angina, arrhythmias (including fatal ventricular fibrillation), cerebral hemorrhage, hypertension, pallor, palpitations, tachyarrhythmia, tachycardia, vasoconstriction, ventricular ectopy, and stress cardiomyopathy

Gastrointestinal Disorders: nausea, vomiting

Infections: Clostridial infections (gas gangrene)

Metabolism and Nutrition Disorders: transient hyperglycemia, sweating

Neurological: disorientation, impaired memory, panic, psychomotor agitations, sleepiness, tingling, weakness, hypoesthesia, dizziness, tremor, headache

Psychiatric: anxiety, apprehensiveness, restlessness

Respiratory: respiratory difficulties

Skin and Subcutaneous Tissue Disorders: bruising, bleeding, discoloration, erythema, necrotizing fasciitis, myonecrosis

7 DRUG INTERACTIONS

7.1 Drugs Increasing Risk of Cardiac Arrhythmias

Observe patients who receive epinephrine while concomitantly taking cardiac glycosides, diuretics, or anti-arrhythmics for the development of cardiac arrhythmias [see Warnings and Precautions (5.3) and Adverse Reactions (6)].

7.2 Drugs Potentiating Effects of Epinephrine

The effects of epinephrine may be potentiated by tricyclic antidepressants, monoamine oxidase inhibitors, levothyroxine sodium, and certain antihistamines, notably chlorpheniramine, tripelennamine, and diphenhydramine, and catechol-O-methyl transferase (COMT) inhibitors such as entacapone.

7.3 Drugs Antagonizing Effects of Epinephrine

The cardiostimulating and bronchodilating effects of epinephrine are antagonized by beta- adrenergic blocking drugs, such as propranolol.

The vasoconstricting and hypertensive effects of epinephrine are antagonized by alpha- adrenergic blocking drugs, such as phentolamine.

Ergot alkaloids may also reverse the pressor effects of epinephrine.

8 USE IN SPECIFIC POPULATIONS

8.1 Pregnancy

Risk Summary

Prolonged experience with epinephrine use in pregnant women over several decades, based on published literature, have not identified a drug associated risk of major birth defects, miscarriage or adverse maternal or fetal outcomes. There are risks to the mother and fetus associated with anaphylaxis. Epinephrine is first-line treatment of anaphylaxis and should not be delayed (see Clinical Considerations). In animal reproductive studies, epinephrine administered by the subcutaneous route to rabbits, mice, and hamsters during the period of organogenesis was teratogenic at doses 7 times and higher than the maximum recommended human intramuscular and subcutaneous dose on a mg/m^2 basis (see Data).

The background risk of major birth defects and miscarriage for the indicated population is unknown. All pregnancies have a background risk of birth defect, loss, or other adverse outcomes. In the U.S. general population, the estimated background risk of major birth defects and miscarriage in clinically recognized pregnancies is 2% to 4% and 15% to 20%, respectively.

Clinical Considerations

Disease-associated maternal and embryo/fetal risk:

During pregnancy, anaphylaxis can be catastrophic and can lead to hypoxic-ischemic encephalopathy and permanent central nervous system damage or death in the mother and, more commonly, in the fetus or neonate. Treatment of anaphylaxis during pregnancy should not be delayed.

Data

Animal Data:

In an embryofetal development study with rabbits dosed during the period of organogenesis, epinephrine was shown to be teratogenic (including gastroschisis and embryonic lethality) at doses approximately 40 times the maximum recommended intramuscular or subcutaneous dose (on a mg/m^2 basis at a maternal subcutaneous dose of 1.2 mg/kg/day for two to three days).

In an embryofetal development study with mice dosed during the period of organogenesis, epinephrine was shown to be teratogenic (including embryonic lethality) at doses approximately 8 times the maximum recommended intramuscular or subcutaneous dose (on a mg/m^2 basis at a maternal subcutaneous dose of 1 mg/kg/day for 10 days). These effects were not seen in mice at approximately 4 times the maximum recommended daily intramuscular or subcutaneous dose (on a mg/m^2 basis at a subcutaneous maternal dose of 0.5 mg/kg/day for 10 days).

In an embryofetal development study with hamsters dosed during the period of organogenesis from gestation days 7 to 10, epinephrine was shown to be teratogenic at doses approximately 7 times the maximum recommended daily intramuscular or subcutaneous dose (on a mg/m^2 basis at a maternal subcutaneous dose of 0.5 mg/kg/day for 4 days).

8.2 Lactation

Risk Summary

There is no information on the presence of epinephrine in human milk, the effects on breastfed infants, or the effects on milk production. However, due to its poor oral bioavailability and short half-life, transfer of epinephrine into breastmilk is expected to be low. Treatment of anaphylaxis in breastfeeding patients should not be delayed.

8.4 Pediatric Use

The safety and effectiveness of AUVI-Q for the emergency treatment of type I allergic reactions, including anaphylaxis have been established in pediatric patients who weigh 7.5 kg or greater. The use of AUVI-Q for this indication is supported by clinical experience. Clinical experience with the use of epinephrine suggests that the adverse reactions seen in pediatric patients are similar in nature and extent to those both expected and reported in adults. Since the doses of epinephrine delivered from AUVI-Q are fixed, use other forms of injectable epinephrine if doses lower than 0.1 mg are deemed necessary.

The safety and effectiveness of AUVI-Q have not been established in pediatric patients who weigh less than 7.5 kg.

8.5 Geriatric Use

Clinical studies of AUVI-Q for emergency treatment of type I allergic reactions, including anaphylaxis, were not conducted to determine whether they respond differently from younger patients. However, other reported clinical experience with use of epinephrine for treatment of anaphylaxis has identified that geriatric patients may be particularly sensitive to the effects of epinephrine. Therefore, these patients may be at greater risk for developing adverse reactions after epinephrine administration [see Overdosage (10)].

10 OVERDOSAGE

Overdosage of epinephrine has been reported to produce extremely elevated arterial pressure, which may result in cerebrovascular hemorrhage, particularly in elderly patients. Overdosage may also result in pulmonary edema because of peripheral vascular constriction together with cardiac stimulation.

Epinephrine overdosage can also cause transient bradycardia followed by tachycardia, which may be accompanied by fatal cardiac arrhythmias; premature ventricular contractions followed by multifocal ventricular tachycardia; atrial tachycardia and occasionally by atrioventricular block; extreme pallor and coldness of the skin; metabolic acidosis; kidney failure.

Epinephrine is rapidly inactivated in the body and treatment following overdosage with epinephrine is primarily supportive. Treatment of epinephrine associated pulmonary edema consists of a rapidly acting alpha-adrenergic blocking drug (such as phentolamine mesylate) and respiratory support. Treatment of epinephrine associated arrhythmias consists of administration of a beta-adrenergic blocking drug (such as propranolol). If necessary, pressor effects may be counteracted by rapidly acting vasodilators or α-adrenergic blocking drugs. If prolonged hypotension follows such measures, it may be necessary to administer another pressor drug.

Consider contacting the Poison Help line (1-800-222-1222) or a medical toxicologist for additional overdosage management recommendations.

11 DESCRIPTION

AUVI-Q (epinephrine injection, USP) 0.3 mg, 0.15 mg and 0.1 mg is an autoinjector and a combination product containing drug and device components.

AUVI-Q includes audible (electronic voice instructions, beeps) and visible (LED lights) cues for use. The needle automatically retracts after the injection is complete.

Each AUVI-Q 0.3 mg delivers a single dose of 0.3 mg epinephrine from epinephrine injection, USP (0.3 mL) in a sterile solution.

Each AUVI-Q 0.15 mg delivers a single dose of 0.15 mg epinephrine from epinephrine injection, USP (0.15 mL) in a sterile solution.

Each AUVI-Q 0.1 mg delivers a single dose of 0.1 mg epinephrine from epinephrine injection, USP (0.1 mL) in a sterile solution.

AUVI-Q 0.3 mg, AUVI-Q 0.15 mg and AUVI-Q 0.1 mg each contain 0.76 mL epinephrine solution. 0.3 mL, 0.15 mL and 0.1 mL epinephrine solution is dispensed for AUVI-Q 0.3 mg, AUVI-Q 0.15 mg and AUVI-Q 0.1 mg, respectively, when activated. The remaining solution is not available for future use and should be discarded.

Each 0.3 mL in AUVI-Q 0.3 mg contains 0.3 mg epinephrine, 2.3 mg sodium chloride, 0.45 mg sodium bisulfite, hydrochloric acid to adjust pH, and water for injection. The pH range is 2.2– 5.0.

Each 0.15 mL in AUVI-Q 0.15 mg contains 0.15 mg epinephrine, 1.2 mg sodium chloride, 0.225 mg sodium bisulfite, hydrochloric acid to adjust pH, and water for injection. The pH range is 2.2–5.0.

Each 0.1 mL in AUVI-Q 0.1 mg contains 0.1 mg epinephrine, 0.78 mg sodium chloride, 0.15 mg sodium bisulfite, hydrochloric acid to adjust pH, and water for injection. The pH range is 2.2–5.0.

Epinephrine is a sympathomimetic catecholamine. Chemically, epinephrine is (-)-3,4-Dihydroxy-a-[(methylamino)methyl]benzyl alcohol with the following structure:

Epinephrine solution deteriorates rapidly on exposure to air or light, turning pink from oxidation to adrenochrome and brown from the formation of melanin.

AUVI-Q is not made with natural rubber latex.

AUVI-Q instructional and safety systems should be thoroughly reviewed with patients and caregivers prior to use [see Patient Counseling Information (17)].

12 CLINICAL PHARMACOLOGY

12.1 Mechanism of Action

Epinephrine acts on both alpha and beta-adrenergic receptors.

Through its action on alpha-adrenergic receptors, epinephrine lessens the vasodilation and increased vascular permeability that occurs during anaphylaxis, which can lead to loss of intravascular fluid volume and hypotension.

Through its action on beta-adrenergic receptors, epinephrine causes bronchial smooth muscle relaxation and helps alleviate bronchospasm, wheezing and dyspnea that may occur during anaphylaxis.

Epinephrine also alleviates pruritus, urticaria, and angioedema and may relieve gastrointestinal and genitourinary symptoms associated with anaphylaxis because of its relaxer effects on the smooth muscle of the stomach, intestine, uterus and urinary bladder.

12.2 Pharmacodynamics

When given subcutaneously or intramuscularly, epinephrine has a rapid onset and short duration of action.

13 NONCLINICAL TOXICOLOGY

13.1 Carcinogenesis, Mutagenesis, Impairment of Fertility

Long-term studies to evaluate the carcinogenic potential of epinephrine have not been conducted.

Epinephrine and other catecholamines have been shown to have mutagenic potential in vitro. Epinephrine was positive in the Salmonella bacterial reverse mutation assay, positive in the mouse lymphoma assay, and negative in the in vivo micronucleus assay. Epinephrine is an oxidative mutagen based on the E. coli WP2 Mutoxitest bacterial reverse mutation assay. This should not prevent the use of epinephrine where indicated [see Indications and Usage (1)].

The potential for epinephrine to impair reproductive performance has not been evaluated, but epinephrine has been shown to decrease implantation in female rabbits dosed subcutaneously with 1.2 mg/kg/day (40-fold the highest human intramuscular or subcutaneous daily dose) during gestation days 3 to 9.

16 HOW SUPPLIED/STORAGE AND HANDLING

How Supplied

AUVI-Q (epinephrine injection) is a clear and colorless solution for intramuscular or subcutaneous use. AUVI-Q is available as an autoinjector as described in Table 2.

Table 2. AUVI-Q Autoinjector Package Configurations and Strengths

Package Configuration | Strength | National Drug Code (NDC)
2 autoinjectors | 0.3 mg/0.3 mL | NDC 60842-023-02
2 autoinjectors | 0.15 mg/0.15 mL | NDC 60842-022-02
2 autoinjectors | 0.1 mg/0.1 mL | NDC 60842-021-02

Storage and Handling

- Protect from light. Epinephrine is light sensitive and should be stored in the outer case.
- Store at 20°C to 25°C (68°F to 77°F); excursions permitted to 15°C to 30°C (59°F to 86°F) [See USP Controlled Room Temperature]. Do not freeze.
- Before using, check to make sure the solution in the autoinjector is clear and colorless. Replace the autoinjector if the solution is discolored, cloudy, or contains particles.

17 PATIENT COUNSELING INFORMATION

Advise the patient to read the FDA-approved patient labeling (Patient Information and Instructions for Use).

Administration and Training

- Instruct patients and/or caregivers in the appropriate use of AUVI-Q. AUVI-Q should be injected into the middle of the outer thigh (through clothing, if necessary). Each device is a single-dose injection.
- Advise patients and/or caregivers when to seek emergency medical care for close monitoring of the type I allergic emergency and in the event that further treatment is required.
- Instruct patients and/or caregivers to inspect the epinephrine solution visually through the viewing window periodically. AUVI-Q should be replaced if the epinephrine solution appears discolored, cloudy, or contains particles.
- Instruct caregivers to hold the leg of young children or infants firmly in place and limit movement prior to and during injection [see Warnings and Precautions (5.1)].
- Instruct patients and/or caregivers that the needle will not be visible after the injection and they may not feel the injection when it occurs.
- Instruct patients and/or caregivers that AUVI-Q includes a 2- second countdown after it is activated and then the voice instructions will indicate when the injection has been completed and to seek medical care, if needed. Instruct patients that AUVI-Q’s black base will lock up onto the device housing and the lights will blink red after the injection has been completed. These post-use indicators help patients and/or caregivers know that AUVI-Q has been activated and an epinephrine injection has been administered.
- Instruct patients and/or caregivers to use and practice with the Trainer to familiarize themselves with the use of AUVI-Q in an allergic emergency. The Trainer may be used multiple times.

Injection-Related Complications

Advise patients to seek immediate medical care in the case of accidental injection into the digits, hands, or feet because such an accidental injection to these areas may cause loss of blood flow to the affected area [see Warnings and Precautions (5.1)].

Serious Infections at the Injection Site

Advise patients that rare cases of serious skin and soft tissue infections, including necrotizing fasciitis and myonecrosis caused by Clostridia (gas gangrene), have been reported at the injection site following epinephrine injection for anaphylaxis. Instruct patients to seek medical care if they develop signs or symptoms of infection, such as persistent redness, warmth, swelling, or tenderness, at the epinephrine injection site [see Warnings and Precautions (5.2)].

Risks Associated with Certain Coexisting Conditions

Advise patients with coexisting conditions (cardiac arrhythmia and ischemia, hypertension, pulmonary edema, hyperthyroidism, renal impairment, Parkinson’s disease, diabetes), for increased risks that may be associated with use of epinephrine [see Warnings and Precautions (5.3)].

Storage and Handling

Epinephrine is light sensitive and should be stored in the outer case provided to protect it from light. Instruct patients that AUVI-Q must be used or properly disposed once the red safety guard is removed [see How Supplied/Storage and Handling (16)].

Manufactured for:
kaleo, Inc.
Richmond, VA 23219 USA
This product may be covered by one or more U.S. patents or pending patent applications; see www.kaleo.com for details. KALÉO® and AUVI-Q® are registered trademarks of kaleo, Inc.
© 2025 kaleo, Inc.

*For California Only: This product uses batteries containing Perchlorate Material – special handling may apply. See www.dtsc.ca.gov/hazardouswaste/perchlorate

PATIENT INFORMATION

AUVI-Q® [Aw-Vee-Kyoo]
(epinephrine injection)
For intramuscular or subcutaneous use
For allergic emergencies (anaphylaxis)

Read this Patient Information leaflet before you have to use AUVI-Q and each time you get a refill. There may be new information. You, your caregiver, or others who may be in a position to administer AUVI-Q should know how to use it before you have an allergic emergency. This information does not take the place of talking with your healthcare provider about your medical condition or your treatment.

What is the most important information I should know about AUVI-Q?

1. Always carry AUVI-Q with you because you may not know when a life-threatening allergic reaction (anaphylactic reaction) may happen. Talk to your healthcare provider if you need additional units to keep at work, school, etc. An anaphylactic reaction is a life-threatening allergic reaction that can happen within minutes and can be caused by stinging and biting insects (bees, wasps, hornets, and mosquitoes), allergy shots, foods, medicines, exercise, or other unknown causes. Follow your healthcare provider’s instructions on when to use AUVI-Q if you have the symptoms of an anaphylactic reaction, which may include the symptoms listed below:
  - trouble breathing
  - wheezing
  - hoarseness (changes in the way your voice sounds)
  - hives (raised reddened rash that may itch)
  - severe itching
  - swelling of your face, lips, mouth or tongue
  - skin rash, redness, or swelling
  - fast heartbeat
  - weak pulse
  - feeling very anxious
  - confusion
  - stomach pain
  - losing control of urine or bowel movements
  - dizziness or fainting
2. Tell your family members and others where you keep AUVI-Q and how to use it before you need it. You may be unable to speak in an allergic emergency.
3. Get medical care for further treatment of the allergic emergency if needed after using AUVI-Q. Before you receive AUVI-Q, your healthcare provider should talk to you about when to get emergency help.

What is AUVI-Q?

- AUVI-Q is a prescription medicine used to treat life-threatening allergic reactions including anaphylaxis in adults and children who weigh 16.5 pounds (7.5 kilograms) or more who are at risk for or have a history of serious allergic reactions.
- AUVI-Q is for immediate self (or caregiver) administration.

It is not known if AUVI-Q is safe and effective in children who weigh less than 16.5 pounds (7.5 kilograms).

What should I tell my healthcare provider before using AUVI-Q?
Before using AUVI-Q, tell your healthcare provider about all of your medical conditions, especially if you:

- have heart problems or high blood pressure.
- have diabetes.
- have thyroid problems.
- have kidney problems.
- have history of depression.
- have Parkinson’s disease.
- are pregnant or plan to become pregnant. It is not known if AUVI-Q will harm your unborn baby.
- are breastfeeding or plan to breastfeed. It is not known if AUVI-Q passes into your breast milk.

Tell your healthcare provider about all the medicines you take,
including prescription and non-prescription medicines, vitamins, and herbal supplements.

AUVI-Q and other medicines may affect each other, causing side effects. AUVI-Q may affect the way other medicines work, and other medicines may affect how AUVI-Q works.

Know the medicines you take. Keep a list of them to show your healthcare provider and pharmacist when you get a new medicine.

How should I use AUVI-Q?

- Read the Instructions for Use at the end of this Patient Information leaflet for information about the right way to use AUVI-Q.
- Use AUVI-Q exactly as your healthcare providers tells you to use it.
- AUVI-Q should only be injected into your outer thigh. If needed, AUVI-Q can be injected through your clothing.
- Each AUVI-Q contains only 1 dose of medicine.
- If a second dose of AUVI-Q is needed, it should be given starting 5 minutes after the first dose.
- You should always carry 2 AUVI-Q devices with you.
- If you need more than 2 doses of epinephrine for a single anaphylaxis episode, more doses must be given by a healthcare provider.
- You may request a Trainer for AUVI-Q. Additional training resources are available at www.auvi-q.com.
  - Practice with the Trainer for AUVI-Q before an allergic emergency happens to familiarize yourself with the use of AUVI-Q in an allergic emergency.
  - The Trainer for AUVI-Q does not contain a needle or medicine and can be reused to practice your injection.
- If you take too much AUVI-Q, call your healthcare provider or Poison Help line at 1-800-222-1222 or go to the nearest hospital emergency room right away.

What are the possible side effects of AUVI-Q?

AUVI-Q may cause serious side effects.

- AUVI-Q should only be injected into your outer thigh. Do not inject AUVI-Q into your:
  - veins
  - buttocks
  - fingers, toes, hands or feet
  If you accidentally inject AUVI-Q into any other part of your body, go to the nearest hospital emergency room right away. Tell the healthcare provider where on your body you received the accidental injection.

- Rarely, patients who use AUVI-Q may develop infections at the injection site within a few days of an injection. Some of these infections can be serious. Call your healthcare provider right away if you have any of the following at an injection site:
  - redness that does not go away
  - swelling
  - tenderness
  - the area feels warm to the touch
- If you inject a young child or infant with AUVI-Q, hold their leg firmly in place before and during the injection to prevent injuries. Ask your healthcare provider to show you how to properly hold the leg of a young child or infant during an injection.
- If you have certain medical conditions, or take certain medicines, your condition may get worse or you may have more or longer lasting side effects when you use AUVI-Q. Talk to your healthcare provider about all your medical conditions.

Common side effects of AUVI-Q include:

- fast, irregular, or ‘pounding’ heart beat
- sweating
- shakiness
- headache
- paleness
- feelings of over excitement, nervousness, or anxiety
- weakness
- dizziness
- nausea and vomiting
- breathing problems

Tell your healthcare provider if you have any side effect that bothers you or that does not go away.

These are not all of the possible side effects of AUVI-Q. For more information, ask your healthcare provider or pharmacist.

Call your doctor for medical advice about side effects. You may report side effects to FDA at 1-800-FDA-1088.

How should I store AUVI-Q?

- Store AUVI-Q at room temperature between 68° to 77°F (20° to 25°C).
- Do not freeze. Do not expose to extreme heat or cold. For example, do not store in your vehicle’s glove box.
- Before using, examine contents in the viewing window. Solution should be clear. If the solution is discolored, cloudy or contains solid particles, replace the autoinjector.
- Your AUVI-Q has an expiration date. Replace it before the expiration date.
- Keep AUVI-Q in the outer case it comes in to protect it from light.

Keep AUVI-Q and all medicines out of the reach of children.

General information about the safe and effective use of AUVI-Q.

Medicines are sometimes prescribed for purposes other than those listed in a Patient Information leaflet. Do not use AUVI-Q for a condition for which it was not prescribed. Do not give AUVI-Q to other people, even if they have the same symptoms that you have. It may harm them.

This Patient Information leaflet summarizes the most important information about AUVI-Q. If you would like more information, talk to your healthcare provider. You can ask your pharmacist or healthcare provider for information about AUVI-Q that is written for health professionals.

What are the ingredients in AUVI-Q?
Active ingredient: epinephrine.
Inactive Ingredients: sodium chloride, sodium bisulfite, hydrochloric acid, and water.

AUVI-Q does not contain latex.

For more information and video instructions on the use of AUVI-Q, go to www.auvi-q.com or call 1-877-302-8847.

Instructions for Use

Read this Instructions for Use carefully before you need to use your AUVI-Q. Before you use AUVI-Q, make sure your healthcare provider shows you the right way to use it. If you have any questions, ask your healthcare provider.

If you are administering AUVI-Q to a young child or infant, hold the leg firmly in place and limit movement prior to and while administering an injection. Ask your healthcare provider to show you how to properly hold the leg in place while administering a dose.

Automated Voice Instructions

AUVI-Q contains an electronic voice instruction system to help guide you through each step of your injection. If the voice instructions do not work for any reason, use AUVI-Q as instructed in these Instructions for Use. It will still work during an allergic reaction emergency.

How to use your AUVI-Q

Figure A.

1. Pull AUVI-Q up from the outer case. See Figure B.
Do not go to step 2 until you are ready to use AUVI-Q. If you are not ready to use AUVI-Q, put it back in the outer case.

Figure B.

2. Pull Red safety guard down and off of AUVI-Q. See Figure C.
To reduce the chance of an accidental injection, do not touch the black base of the auto-injector, which is where the needle comes out. If an accidental injection happens, get medical help right away.

Note: The red safety guard is made to fit tight. Pull firmly to remove.

Figure C.

3. Place black end of AUVI-Q against the middle of the outer thigh (through clothing, if needed), then push firmly until you hear a click and hiss sound, and hold in place for 2 seconds. See Figure D.

Only inject into the middle of the outer thigh. Do not inject into any other part of the body.

If you are administering AUVI-Q to a young child or infant, hold the leg firmly in place while administering an injection See Figure E.

Figure D.

(For AUVI-Q 0.3 mg and AUVI-Q 0.15 mg)

Figure E.

(For AUVI-Q 0.1 mg)

Note: AUVI-Q makes a distinct sound (click and hiss) when you push it firmly against your outer thigh. This is normal and indicates AUVI-Q is working correctly. Do not pull AUVI-Q away from your leg when you hear the click and hiss sound.

The needle automatically retracts after the injection is complete, so the needle will not be visible after the injection. AUVI-Q includes a 2-second countdown after it is activated, then the voice instruction will indicate the injection is complete, and to seek medical care if needed. AUVI-Q will beep, and the lights will blink red.

4. Get medical care for further treatment of the allergic emergency if needed after using AUVI-Q.

Before you receive AUVI-Q, your healthcare provider should talk to you about when to get emergency help.

Replace the outer case and talk to your healthcare provider about the right way to throw away your AUVI-Q.

Ask your healthcare provider for an AUVI-Q prescription refill.
After the use of AUVI-Q:

- The black base will lock into place.
- The voice instruction system will say “seek medical care if needed”, say “this AUVI-Q has been used…”, and the lights will blink red.
- Do not replace the red safety guard.
- The viewing window will no longer be clear.
- It is normal for some medicine to remain in your AUVI-Q after you have received your dose of medicine.
- Talk to your healthcare provider about the right way to throw away your AUVI-Q.
- AUVI-Q is a single-dose auto-injector and cannot be reused. AUVI-Q must be used or properly disposed after the red safety guard is removed.

Until you throw away your used AUVI-Q, the electronic voice instruction system will remind you that it has been used when the outer case is removed.

This Patient Information and Instructions for Use has been approved by the U.S. Food and Drug Administration

Revised: Apr 2025

Manufactured for:
kaleo, Inc.
Richmond, VA 23219 USA
This product may be covered by one or more U.S. patents or pending patent applications; see www.kaleo.com for details. KALÉO® and AUVI-Q® are registered trademarks of kaleo, Inc.
© 2025 kaleo, Inc.

*For California Only: This product uses batteries containing Perchlorate Material – special handling may apply. See www.dtsc.ca.gov/hazardouswaste/perchlorate

TRAINER FOR AUVI-Q®
Trainer Instructions for Use

Important:
The TRAINER for AUVI-Q Does Not contain a needle or medicine.

In case of an allergic emergency, use the real AUVI-Q and not the gray Trainer.
Always carry your real Auvi-Q with you in case of an allergic emergency.

Important Information about the TRAINER for AUVI-Q:

Inside your TRAINER for AUVI-Q are:

- batteries
- a speaker that will make a beeping sound and that produces electronic voice instructions
- red and green blinking lights

The TRAINER for AUVI-Q batteries are made to last long enough for you to practice 1 time each day for 2 years. If your TRAINER for AUVI-Q does not work properly call your healthcare provider for a new Trainer.

What is the TRAINER for AUVI-Q?

- The TRAINER for AUVI-Q does not contain a needle or medicine and can be reused to practice your injection.
- Practice with the TRAINER for AUVI-Q before an allergic emergency happens to make sure you are able to safely use the real AUVI-Q in an emergency.

Your TRAINER for AUVI-Q
Figure A

TRAINER for AUVI-Q
Top view

AUVI-Q
AUVI-Q 0.3 mg is orange
AUVI-Q 0.15 mg is blue
AUVI-Q 0.1 mg is white and lavender

TRAINER for AUVI-Q:

- is inside a gray outer case
- does not have a needle or medicine inside
- can be reused (the red safety guard can be placed back on the base of the Trainer after use)
- has no expiration date
- has embossed “TRAINER” on top of the device

AUVI-Q:

- is inside an orange (0.3 mg) or blue (0.15 mg) or white and lavender (0.1 mg) outer case
- contains a needle and epinephrine medicine
- cannot be reused (AUVI-Q must be used or properly disposed once the red safety guard is removed)
- has a medicine expiration date listed on the device

In case of an allergic emergency, use the real AUVI-Q and not the gray Trainer.

Who should practice using the TRAINER for AUVI-Q?
Anyone who may need to help you with AUVI-Q in case of an allergic emergency:

- You
- Caregivers
- Family
- Friends
- Co-workers
- Teachers
- Child Care or Day Care Workers

Have them practice using the Trainer and review the Patient Information Leaflet included in the packaging with each prescription of AUVI-Q.
For more information and video instructions on the use of AUVI -Q, go to www.AUVI-Q.com or call 1-877-302-8847.

Practicing with the TRAINER for AUVI-Q
Practice with the TRAINER for AUVI-Q before an allergic emergency happens to make sure you are able to safely use the real AUVI-Q in an emergency.

- You should practice daily for the first week after you receive your TRAINER for AUVI-Q to help you feel comfortable using AUVI-Q quickly and safely. Even when you are comfortable using the Trainer, continue to practice using it often.

How to Use the Trainer

How the TRAINER for AUVI-Q works
Although the Trainer does not have a needle and contains no medicine, it works the same way as the real AUVI-Q.
As with the real AUVI-Q, the TRAINER for AUVI-Q contains an electronic voice instruction system to help guide you through each step of your injection. If the voice instructions do not work for the TRAINER for AUVI-Q for any reason, you can still use the TRAINER for AUVI-Q as instructed in this leaflet to practice.
The TRAINER for AUVI-Q has the same blinking red and green lights as the real AUVI-Q.
As with the real AUVI-Q, if practicing with a young child or infant, hold the leg firmly in place while using the TRAINER for AUVI-Q. Ask your healthcare provider to show you how to properly hold the leg to practice so that you will be prepared before an allergic emergency happens.

Follow These Steps

1.Pull the TRAINER for AUVI-Q from the outer case. See Figure B

2. Pull Red safety guard down and off of the Trainer. See Figure C.

Figure B

Figure C

Note: The red safety guard is made to fit tight similar to the safety guard on the real AUVI-Q. Pull firmly to remove.

3. Place black end against the middle of the outer thigh (through clothing, if needed), then push firmly until you hear a click and hiss sound, and hold in place for 2 seconds. See Figure D.
As with the real AUVI-Q, if practicing with a young child or infant, hold the leg firmly in place while using the TRAINER for AUVI-Q. (See Figure E).

Figure D

Figure E

Note: In an actual emergency, after the injection you would seek medical care if needed.
Only practice using the middle of your outer thigh. The outer thigh is where you would inject with the real AUVI-Q.
Note: The TRAINER for AUVI-Q makes a distinct sound (click and hiss) when you push it firmly against your outer thigh. This is the same sound that is made with the real AUVI-Q. This is normal, and indicates AUVI-Q is working correctly. Do not pull AUVI-Q away from your leg when you hear the click and hiss sound.

4. After practicing, reset the TRAINER for AUVI-Q:
a. Replace the Red safety guard. Do not hold the black base while inserting the Red safety guard. The Black base will drop down into its original location during Red safety guard insertion. See Figure F.
b. Slide the TRAINER for AUVI-Q all the way back into the gray outer case to reset the electronic voice system. See Figure G.

Figure F

Figure G

Note: Leave the TRAINER for AUVI-Q in its outer case for at least 5 seconds between each time you practice to allow the electronic voice system to reset.

Storage:

- Store the TRAINER for AUVI-Q at room temperature; the TRAINER for AUVI-Q should not be used at temperatures less than 50°F (10°C) or greater than 104°F (40°C).
- Store the TRAINER for AUVI-Q in its outer case.
- Keep the TRAINER for AUVI-Q away from dirt, chemicals, and water.

Disposal:
The TRAINER for AUVI-Q contains electronics and lithium coin cell batteries, and should be disposed of in the correct manner. Follow your State and local environmental regulations for disposal.

For California Only: This product uses batteries containing Perchlorate Material - special handling may apply. See www.dtsc.ca.gov/hazardouswaste/perchlorate

Manufactured for:
kaleo, Inc.
Richmond, VA 23219 USA

This product may be covered by one or more U.S. patents or pending patent applications; see www.kaleo.com for details. KALÉO® and AUVI-Q® are registered trademarks of kaleo, Inc.
© 2025 kaleo, Inc.

Rev. Apr 2025